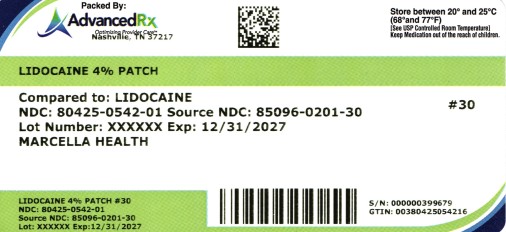 DRUG LABEL: LIDOCAINE 4%
NDC: 80425-0542 | Form: PATCH
Manufacturer: Advanced Rx of Tennessee, LLC
Category: otc | Type: HUMAN OTC DRUG LABEL
Date: 20250808

ACTIVE INGREDIENTS: LIDOCAINE 400 mg/10 g
INACTIVE INGREDIENTS: TITANIUM DIOXIDE; PROPYLENE GLYCOL; GLYCERIN; POVIDONE K90; KAOLIN; TARTARIC ACID; SODIUM POLYACRYLATE (2500000 MW); DIHYDROXYALUMINUM AMINOACETATE ANHYDROUS; METHYLPARABEN; EDETATE DISODIUM; POLYSORBATE 80; HYDROXYACETOPHENONE; PROPYLPARABEN; WATER

Lidocaine 4% Patch #30

ACTIVE INGREDIENTS

Lidocaine 4% w/w

OTHER INGREDIENTS

Dihydroxyaluminum Aminoacetate, Edetate Disodium, Glycerin, Kaolin, Methylparaben, Polysorbate 80, Propylene Glycol, Polyacrylic Acid, Polyvinylpyrrolidone K90, Propylparaben, Sodium Polyacrylate, Tartaric Acid, Titanium Dioxide, Water.

PURPOSE & USE

External Anesthetic- For temporary relief of pain

WARNINGS

For external use only.

Dosage & Administration

Adults and Children 12 Years of Age or Over:

- Apply one 4% lidocaine patch at a time to the affected area.
- Use up to 3 times daily, with each application lasting no more than 8 hours.
- Clean and dry the skin before applying the patch.
- Remove the patch after the specified duration and reseal the pouch containing unused patches.

Children Under 12 Years of Age: Consult a doctor for use.

Precautions:

- Avoid applying to broken or irritated skin.
- Do not apply more than one patch at a time.
- Avoid using local heat sources on the area where the patch is applied.

DO NOT USE

- on the face or rashes, on wounds or damaged skin
- in the eyes, mouth, or other mucous membranes
- on genitals
- with a heating pad
- right before or after heart surgery
- any patch from a pouch that has been opened for 7 or more days
- in large quantities, particularly over raw surfaces or blistered areas
- if tamper-evident seal is torn, broken, or missing
- more than 2 patches per day unless directed by a doctor
- children under 18 years of age

Ask a doctor before use if you have:

- allergies to topical products
- high blood pressure, heart disease, or kidney disease

When using this product, avoid contact with eyes. If eye contact occurs, rinse thoroughly with water.

The risk of heart attack or stroke may increase if you use more than directed or for longer than directed.

Stop use and ask doctor if condition worsens, or if symptoms persist for more than 7 days or clear up and occur again within a few days.

If pregnant of breast-feeding, ask a health professional before use

Do not use during last 3 months of pregnancy because it may cause problems in the unborn child or complications during delivery.

Keep out of reach of children.

If put in mouth, seek medical help or contact a Poison Control Center right away.

Dispose if the used patches by folding sticky ends together.

Uses:

For temporary relief of pain

WHEN USING THIS PRODUCT

- Use only as directed
- Avoid contact with the eyes, mucous membranes or rashes
- Do not bandage

STOP USE ... IF

- Localized skin reactions occur, such as rash, itching, redness, irritation, pain, swelling and blistering
- Conditions worsen
- Symptoms persists for more than 7 days
- Symptoms clear up and occur again within a few days

CONSULT WITH A DOCTOR OR PHARMACIST BEFORE CONTINUED USE IF

- Localized skin reactions occur, such as rash, itching, redness, irritation, pain, swelling and blistering
- Conditions worsen
- Symptoms persists for more than 7 days
- Symptoms clear up and occur again within a few days

IF YOU ARE PREGNANT OR BREAST-FEEDING

ALWAYS FIRST CONSULT WITH A HEALTH PROFESSIONAL

KEEP OUT OF THE REACH OF CHILDREN

If swallowed, get medical help or contact a Poison Control Center right away.

OTHER INFORMATION

- Some individuals may not experience pain relief until several minutes or hours after applying the patch
- Avoid storing product in direct sunlight
- Protect product from excessive moisture

QUESTIONS?

Call toll-free: (307) 410-3813 or Email: info@marcellahealth.com